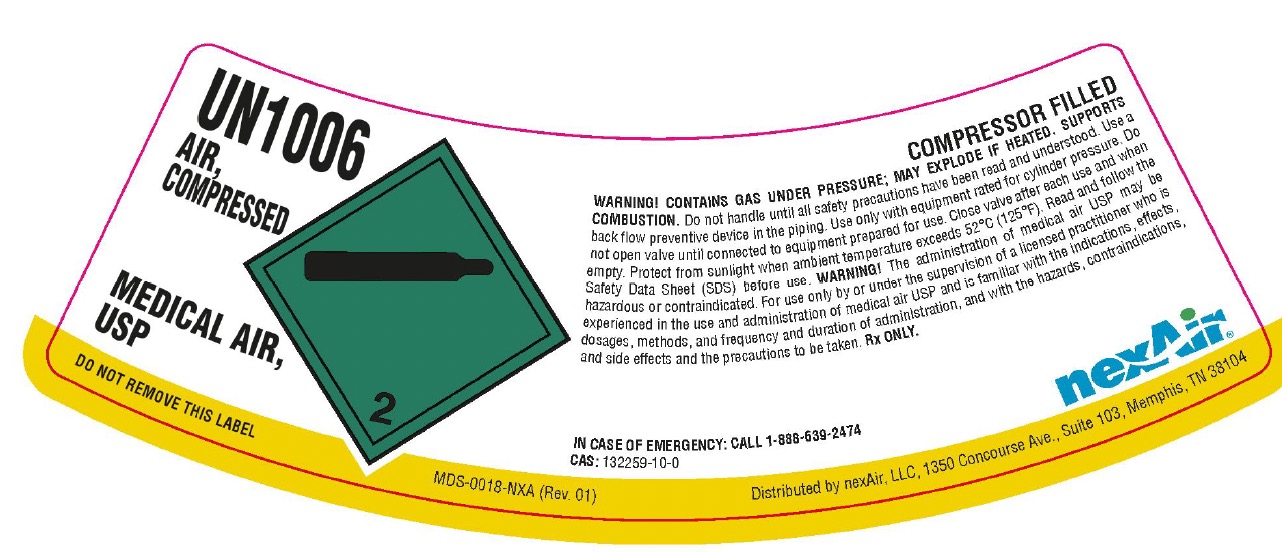 DRUG LABEL: Air
NDC: 12213-711 | Form: GAS
Manufacturer: NexAir, LLC
Category: animal | Type: PRESCRIPTION ANIMAL DRUG LABEL
Date: 20251111

ACTIVE INGREDIENTS: Air 1000 mL/1 L

Air Label

PACKAGE LABEL

UN1006
AIR, COMPRESSED
MEDICAL AIR, USP
DO NOT REMOVE THIS LABEL
COMPRESSOR FILLED
WARNING! CONTAINS GAS UNDER PRESSURE; MAY EXPLODE IF HEATED. SUPPORTS COMBUSTION. Do not handle until all safety precautions have been read and understood. Use a back flow preventive device in the piping. Use only with equipment rated for cylinder pressure. Do not open valve until connected to equipment prepared for use. Close valve after each use and when empty. Protect from sunlight when ambient temperature exceeds 52 C (125 F). Read and follow the Safety Data Sheet (SDS) before use. WARNING! The administration of medical air USP may be hazardous or contraindicated. For use only by or under the supervision of a licensed practitioner who is experienced in the use and administration of medical air USP and is familiar with the indications, effects, dosages, methods, and frequency and duration of administration, and with the hazards, contraindications, and side effects and the precautions to be taken. Rx ONLY.
IN CASE OF EMERGENCY: CALL 1-888-639-2474
CAS: 132259-10-0
nexAir
Distributed by nexAir, LLC, 1350 Concourse Ave., Suite 103, Memphis, TN 38104